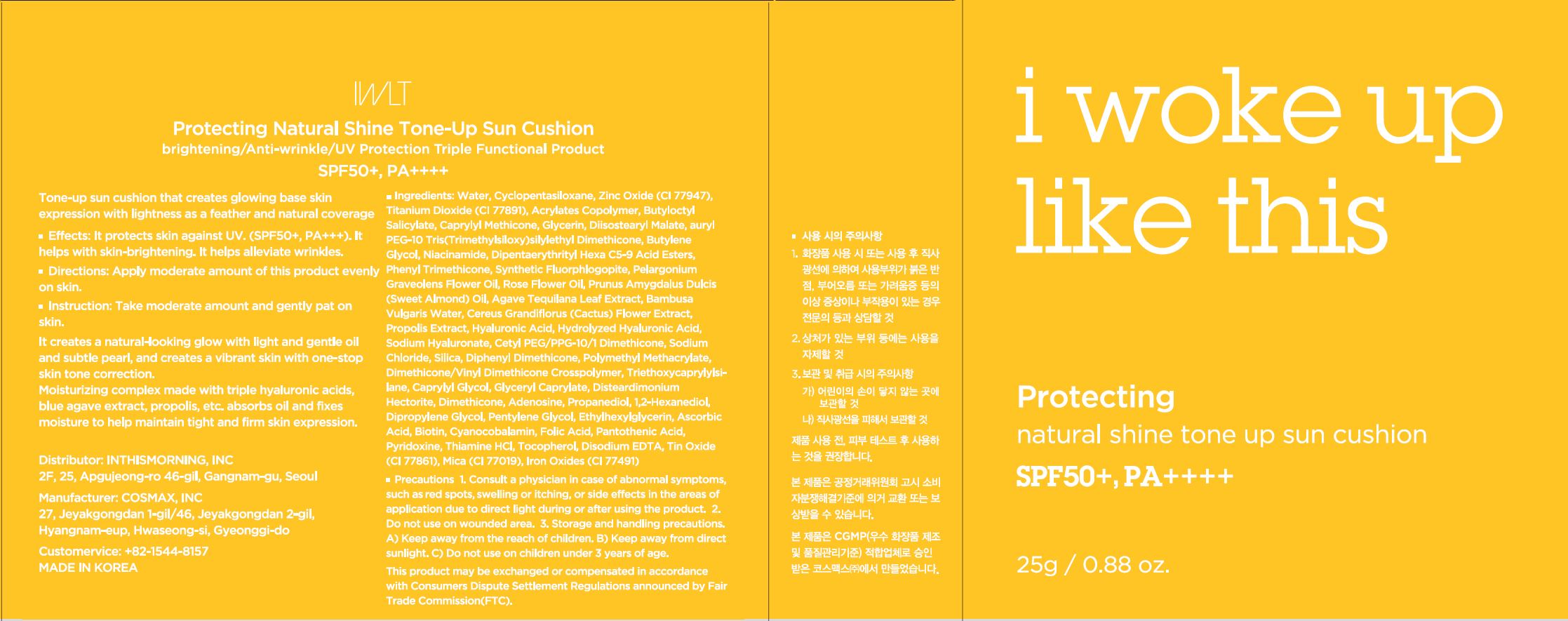 DRUG LABEL: protecting natural shine tone up sun cushion refill
NDC: 71217-0045 | Form: POWDER
Manufacturer: In This Morning
Category: otc | Type: HUMAN OTC DRUG LABEL
Date: 20200210

ACTIVE INGREDIENTS: ADENOSINE 0.04 g/100 g; NIACINAMIDE 2 g/100 g; ZINC OXIDE 9.699515 g/100 g; TITANIUM DIOXIDE 7.383 g/100 g
INACTIVE INGREDIENTS: WATER; BUTYLENE GLYCOL

Drug Facts

ACTIVE INGREDIENT

niacinamide, adenosine, titanium dioxide, zinc oxide

INACTIVE INGREDIENT

water, butylene glycol, etc.

PURPOSE

against UV, skin-brightening, alleviate wrinkles

keep out or reach of the children

INDICATIONS AND USAGE

apply moderate amount of this product evenly on skin

WARNINGS

1. Do not use in the following cases(Eczema and scalp wounds)
2.Side Effects
1)Due to the use of this druf if rash, irritation, itching and symptopms of hypersnesitivity occur dicontinue use and consult your phamacisr or doctor
3.General Precautions
1)If in contact with the eyes, wash out thoroughty with water If the symptoms are servere, seek medical advice immediately
2)This product is for exeternal use only. Do not use for internal use
4.Storage and handling precautions
1)If possible, avoid direct sunlight and store in cool and area of low humidity
2)In order to maintain the quality of the product and avoid misuse
3)Avoid placing the product near fire and store out in reach of children

DOSAGE AND ADMINISTRATION

for external use only